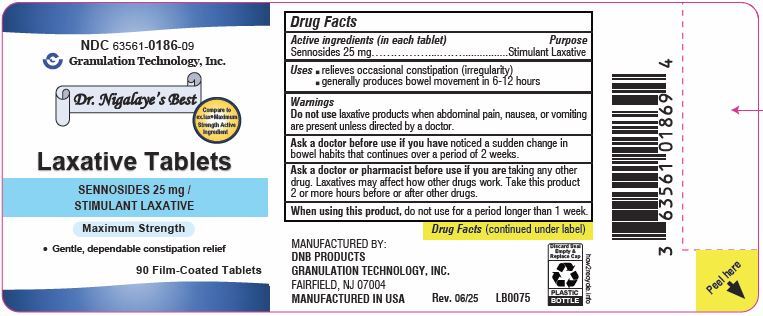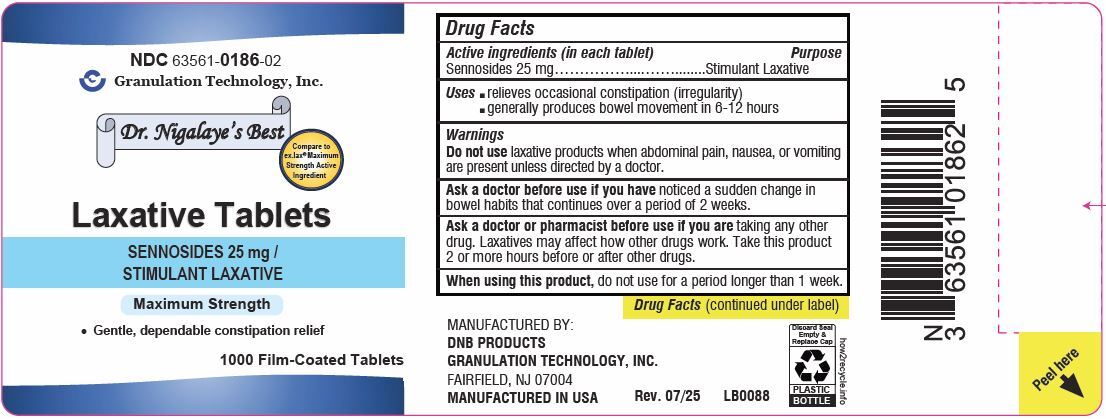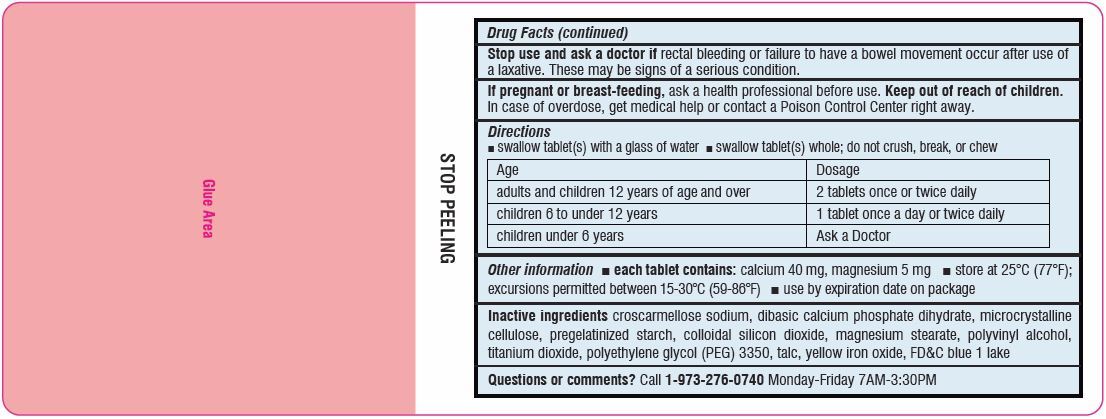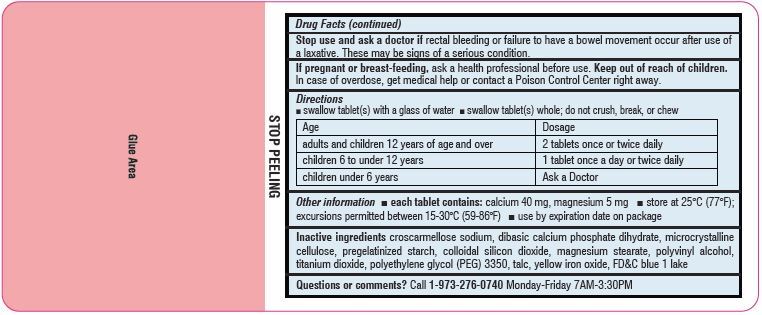 DRUG LABEL: Laxative
NDC: 63561-0186 | Form: TABLET, FILM COATED
Manufacturer: Granulation Technology, Inc.
Category: otc | Type: HUMAN OTC DRUG LABEL
Date: 20250730

ACTIVE INGREDIENTS: SENNOSIDES 25 mg/1 1
INACTIVE INGREDIENTS: CROSCARMELLOSE SODIUM; DIBASIC CALCIUM PHOSPHATE DIHYDRATE; CELLULOSE, MICROCRYSTALLINE; STARCH, CORN; SILICON DIOXIDE; MAGNESIUM STEARATE; POLYVINYL ALCOHOL; TITANIUM DIOXIDE; POLYETHYLENE GLYCOL 3350; TALC; FERRIC OXIDE YELLOW; FD&C BLUE NO. 1 ALUMINUM LAKE

Laxative Tablets
SENNOSIDES, 25 mg
STIMULANT LAXATIVE

Drug Facts

Active ingredient (in each tablet)
Sennosides, 25 mg

Purpose

Stimulant Laxative

Uses

- Relieves occasional constipation (irregularity)
- Generally produces a bowel movement in 6-12 hours

Do not use laxative products when abdominal pain, nausea, or vomiting are present unless directed by a doctor.

Ask a doctor before use if you have noticed a sudden change in bowel habits that persists over a period of two weeks.

Ask a doctor or pharmacist before use if you are taking any other drug. Laxatives may affect how other drugs work. Take this product two or more hours before or after other drugs.

When using this product do not use for a period longer than one week.

Stop use and ask a doctor if rectal bleeding or failure to have a bowel movement occur after use of a laxative. These may be signs of a serious condition.

PREGNANCY OR BREAST FEEDING

If pregnant or breast-feeding, ask a health professional before use.

Inactive ingredients

croscarmellose sodium, dibasic calcium phosphate dihydrate, microcrystalline cellulose, pregelatinized starch, colloidal silicon dioxide, magnesium stearate, polyvinyl alcohol, titanium dioxide, polyethylene glycol (PEG) 3350, talc, yellow iron oxide, FD&C blue 1 lake

Keep out of reach of children. In case of overdose, get medical help or contact a Poison Control Center right away (1-800-222-1222).

Directions

- swallow tablet (s) with a glass of water.
- swallow tablet (s) whole, do not crush, break, or chew.

Age | Dosage
adults and children 12 years of age and over | 2 tablets once or twice daily
children 6 to under 12 years | 1 tablet once a day or twice daily
children under 6 years | Ask a doctor

Other information

- Each tablet contains: Calcium 40 mg, Magnesium 5 mg
- Store at 25°C (77°F); excursions permitted between 15°-30°C (59°-86°F)
- Use by expiration date on package

Questions or comments?

call 1-973-276-0740

Principal Display Panel

NDC 63561-0186-09

Laxative Tablets Label

SENNOSIDES, 25 mg / STIMULANT LAXATIVE

Compare to ex.lax® Maximum Strength Active Ingredient

90 Film-Coated Tablets

NDC 63561-0186-02

Laxative Tablets Label

SENNOSIDES, 25 mg / STIMULANT LAXATIVE

Compare to ex.lax ® Maximum Strength Active Ingredient

1000 Film-Coated Tablets